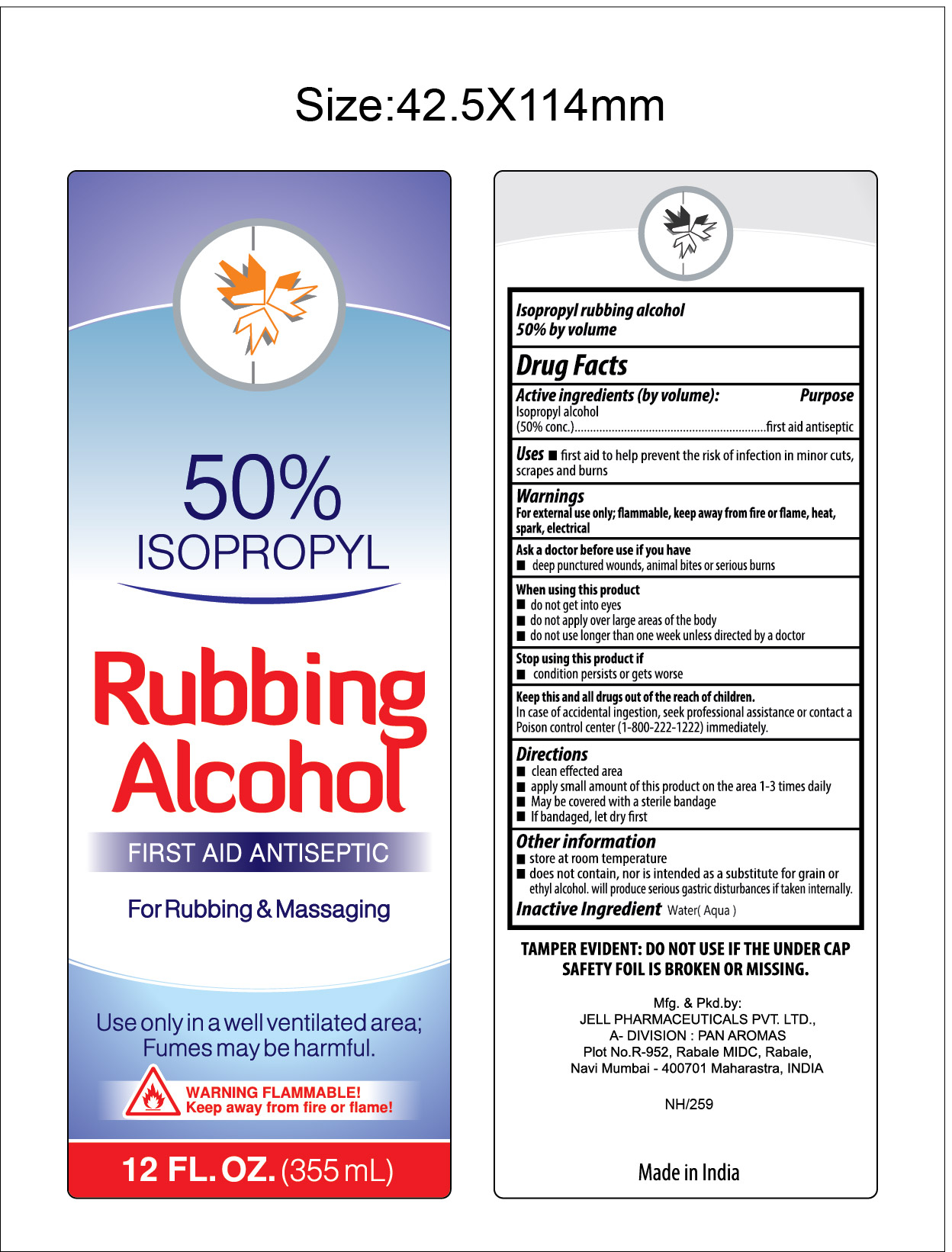 DRUG LABEL: Isopropyl Rubbing Alcohol
NDC: 30400-100 | Form: LIQUID
Manufacturer: Jell Pharmaceuticals Pvt. Ltd.
Category: otc | Type: HUMAN OTC DRUG LABEL
Date: 20251111

ACTIVE INGREDIENTS: ISOPROPYL ALCOHOL 50 mL/100 mL
INACTIVE INGREDIENTS: WATER

Isopropyl Rubbing Alcohol

Active Ingredients

Isopropyl alcohol (50% conc.)

Purpose

First aid antiseptic

Uses

First aid to help prevent the risk of infection in minor cuts, scrapes and burns

Warnings

For external use only

- flammable, keep away from fire or flame, heat, spark, electrical

Ask a doctor before use if you have

- deep puncture wounds, animal bites or serious burns

When using this product

- do not get into eyes
- do not apply over large areas of body
- do not use longer than one week unless directed by a doctor

Stop using this product if

- condition persists or gets worse

Keep this and all drugs out of the reach of children

In case of accidental ingestion, seek professional assistance or contact a Poison control center (1-800-222-1212) immediately

Directions

- clean affected area
- apply a small amount of this product on the area 1-3 times daily
- may be covered with a sterile bandage
- if bandaged, let dry first

Inactive ingredient

purified water